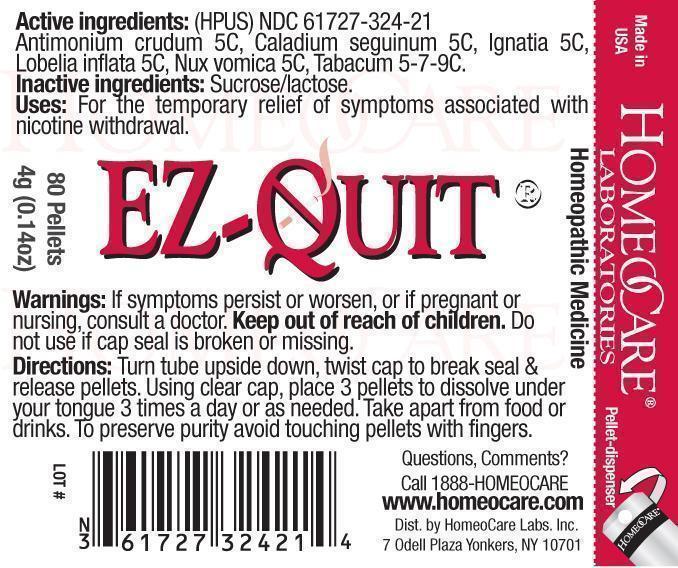 DRUG LABEL: EZ-Quit
NDC: 61727-324 | Form: PELLET
Manufacturer: Homeocare Laboratories
Category: homeopathic | Type: HUMAN OTC DRUG LABEL
Date: 20181231

ACTIVE INGREDIENTS: ANTIMONY TRISULFIDE 5 [hp_C]/4 g; DIEFFENBACHIA SEGUINE 5 [hp_C]/4 g; STRYCHNOS IGNATII SEED 5 [hp_C]/4 g; LOBELIA INFLATA 5 [hp_C]/4 g; STRYCHNOS NUX-VOMICA SEED 5 [hp_C]/4 g; TOBACCO LEAF 9 [hp_C]/4 g
INACTIVE INGREDIENTS: SUCROSE; LACTOSE

EZ-Quit

Active ingredients:

(HPUS) Antimonium crudum 5C, Caladium seguinum 5C, Ignatia 5C, Lobelia inflata 5C, Nux vomica 5C, Tabacum 5-7-9C.

Inactive ingredients:

Sucrose/lactose.

Purpose:

For the temporary relief of symptoms associated with nicotine withdrawal.

Warnings:

If symptoms persist or worsen, or if pregnant or nursing, consult a doctor. Keep out of reach of children. Do not use if cap seal is broken or missing.

Dosage & Administration:

Turn tube upside down, twist cap to break seal & release pellets. Using clear cap, place 3 pellets to dissolve under your tongue 3 times a day or as needed. Take apart from food or drinks. To preserve purity avoid touching pellets with fingers.

Indications & Usage:

Turn tube upside down, twist cap to break seal & release pellets. Using clear cap, place 3 pellets to dissolve under your tongue 3 times a day or as needed. Take apart from food or drinks. To preserve purity avoid touching pellets with fingers.

Keep out of reach of children.

EZ-Quit

Homeopathic Medicine

80 Pellets

hcl_label_ezquit-2012.jpg